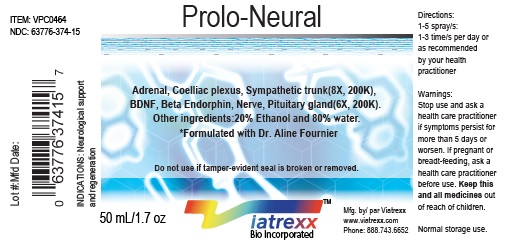 DRUG LABEL: Viatrexx-Prolo-Neural
NDC: 63776-374 | Form: SPRAY
Manufacturer: VIATREXX BIO INCORPORATED
Category: homeopathic | Type: HUMAN OTC DRUG LABEL
Date: 20190319

ACTIVE INGREDIENTS: Sus Scrofa Adrenal Gland 200 [kp_C]/1 mL; Bos Taurus Adrenal Gland 200 [kp_C]/1 mL; Brain-Derived Neurotrophic Factor Human 200 [kp_C]/1 mL; Beta-Endorphin Human 200 [kp_C]/1 mL; Bos Taurus Solar Plexus 200 [kp_C]/1 mL; Sus Scrofa Solar Plexus 200 [kp_C]/1 mL; Sus Scrofa Nerve 200 [kp_C]/1 mL; Bos Taurus Nerve 200 [kp_C]/1 mL; Sus Scrofa Pituitary Gland 200 [kp_C]/1 mL; Bos Taurus Pituitary Gland 200 [kp_C]/1 mL; Sus Scrofa Sympathetic Nerve 200 [kp_C]/1 mL; Bos Taurus Sympathetic Nerve 200 [kp_C]/1 mL
INACTIVE INGREDIENTS: Alcohol; Water

Prolo-Neural

Active Ingredients

Adrenal (8X, 200K), BDNF (6X, 200K), Beta Endorphin (6X, 200K), Coelliac plexus (8X, 200K), Nerve (6X, 200K), Pituitary gland (6X, 200K), Sympathetic trunk (8X, 200K).

Purpose

Adrenal
BDNF
Beta Endorphin
Coelliac plexus
Nerve
Pituitary gland
Sympathetic trunk

Adrenal support
Regeneration
Pain relief
Neurological
Regeneration
Regeneration
Neurological

Description

Viatrexx-Prolo-Neural is a homeopathic product composed of physiological (low dose and low low dose) natural micro nutrients. These micro particles are designed to nourish the system.

Uses

Neurological support and regeneration

Warnings

Stop use and ask a health care practitioner if symptoms persist for more than 5 days or worsen. If pregnant or breastfeeding, ask a health care practitioner before use.

Dosage

1-3 spray(s); 1-3 time(s) per day or as recommended by your health care practitioner.

Inactive Ingredients

Alcohol 20% and Water 80%

Product Availability

Product may be acquired in 0.5, 30 ,50, 100, 250 mL bottles.

PACKAGE LABEL.PRINCIPAL DISPLAY PANEL

NDC: 63776-374-11
Item: VSPC0464
Viatrexx Bio Incorporated
Viatrexx-Prolo-Neural
Box of 1 X 0.5 mL ampule
For Oral and Topical Use
Expiry date: Lot #:
Manufactured for:
Viatrexx Bio Incorporated Newark, DE, USA, 19713
www.Viatrexx.com
Ingredients, homeopathic
See insert or www.viatrexx.com
Inactives: Alcohol 20%, Water

NDC: 63776-374-14
Item: VSPC0464
Viatrexx Bio Incorporated
Viatrexx-Prolo-Neural
Box of 1 X 30 mL spray bottle
For Oral and Topical Use
Expiry date: Lot #:
Manufactured for:
Viatrexx Bio Incorporated Newark, DE, USA, 19713
www.Viatrexx.com
Ingredients, homeopathic
See insert or www.viatrexx.com
Inactives: Alcohol 20%, Water

NDC: 63776-374-15
Item: VSPC0464
Viatrexx Bio Incorporated
Viatrexx-Prolo-Neural
Box of 1 X 50 mL spray bottle
For Oral and Topical Use
Expiry date: Lot #:
Manufactured for:
Viatrexx Bio Incorporated Newark, DE, USA, 19713
www.Viatrexx.com
Ingredients, homeopathic
See insert or www.viatrexx.com
Inactives: Alcohol 20%, Water

NDC: 63776-374-16
Item: VSPC0464
Viatrexx Bio Incorporated
Viatrexx-Prolo-Neural
Box of 1 X 100 mL bottle
For Oral and Topical Use
Expiry date: Lot #:
Manufactured for:
Viatrexx Bio Incorporated Newark, DE, USA, 19713
www.Viatrexx.com
Ingredients, homeopathic
See insert or www.viatrexx.com
Inactives: Alcohol 20%, Water

NDC: 63776-374-17
Item: VSPC0464
Viatrexx Bio Incorporated
Viatrexx-Prolo-Neural
Box of 1 X 250 mL bottle
For Oral and Topical Use
Expiry date: Lot #:
Manufactured for:
Viatrexx Bio Incorporated Newark, DE, USA, 19713
www.Viatrexx.com
Ingredients, homeopathic
See insert or www.viatrexx.com
Inactives: Alcohol 20%, Water